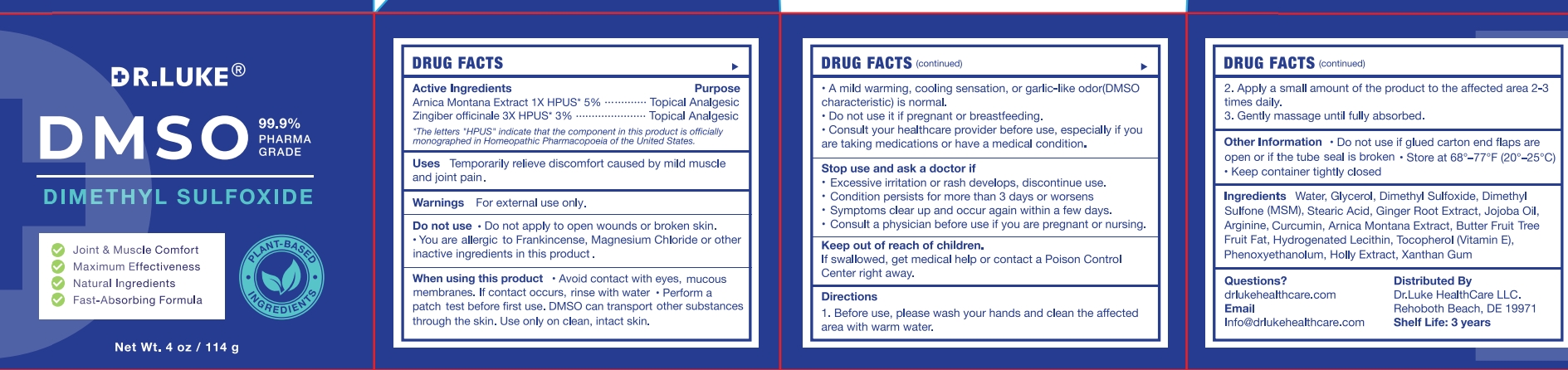 DRUG LABEL: Dr. Luke DMSO Cream
NDC: 87147-006 | Form: CREAM
Manufacturer: DANOUS LAND FLOOW LLC
Category: otc | Type: HUMAN OTC DRUG LABEL
Date: 20251119

ACTIVE INGREDIENTS: ARNICA MONTANA 1 g/100 g
INACTIVE INGREDIENTS: HYDROGENATED SOYBEAN LECITHIN; XANTHAN GUM; DIMETHYL SULFONE; WATER; GLYCERIN; DIMETHYL SULFOXIDE; MAGNESIUM CHLORIDE; STEARIC ACID; JOJOBA OIL; ARGININE; FRANKINCENSE; CURCUMIN

ACTIVE INGREDIENT

Arnica Montana Extract 1X HPUS 5%
Zingiber officinale 3XHPUS 3%

PURPOSE

Topical Analgesic

INDICATIONS AND USAGE

Temporarily relieve discomfort caused by mild muscle and joint pain

WARNINGS

- For external use only.

DO NOT USE

- Do not apply to open wounds or broken skin.
- You are allergic to Frankincense, Magnesium Chloride or other inactive ingredients in this product

WHEN USING

- Avoid contact with eyes, mucous membranes. If contact occurs, rinse with water
- Perform a patch test before first use.DMSO can transport other substances through the skin. Use only on clean, intact skin.
- A mild warming, cooling sensation, or garlic-like odor(DMSO characteristic) is normal.
- Do not use it if pregnant or breastfeeding.
- Consult your healthcare provider before use, especially if you are taking medications or have a medical condition.

- excessive irritation or rash develops, discontinue use.
- condition persists for more than 3 days or worsens
- symptoms clear up and occur again within a few days.

ASK DOCTOR/PHARMACIST

consult a physician before use if you are pregnant or nursing.

KEEP OUT OF REACH OF CHILDREN

If swallowed, get medical help or contact a Poison Control Center right away.

INSTRUCTIONS FOR USE

Before use, Please wash your hands and clean the affected area with warm water.
Apply a small amount of the product to the affected area 2-3 times daily.
Gently massage until fully absorbed.

INACTIVE INGREDIENT

Water
Glycerol
Dimethyl Sulfoxide
Dimethyl Sulfone
Magnesium Chloride
Stearic Acid
Jojoba Oil
Arginine
Curcumin
Frankincense Extract
Hydrogenated Lecithin
Vitamin E
Xanthan Gum

- Do not use if glued carton end flaps are open or if the tube seal is broken.
- Store at 68°-77°F (20°-25C).
- Keep container tightly closed

DOSAGE AND ADMINISTRATION

Apply a small amount of the product to the affected area 2-3 times daily.